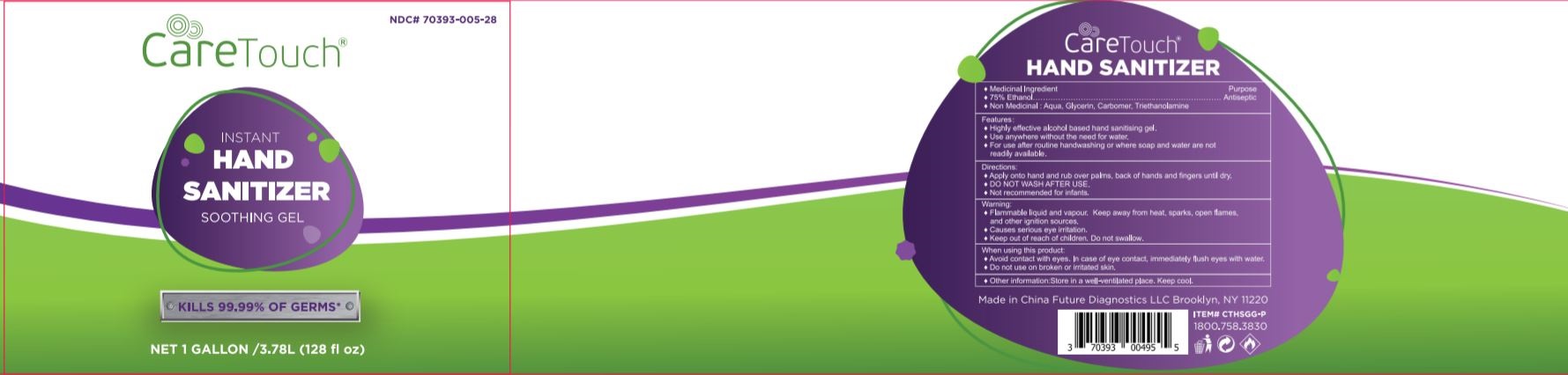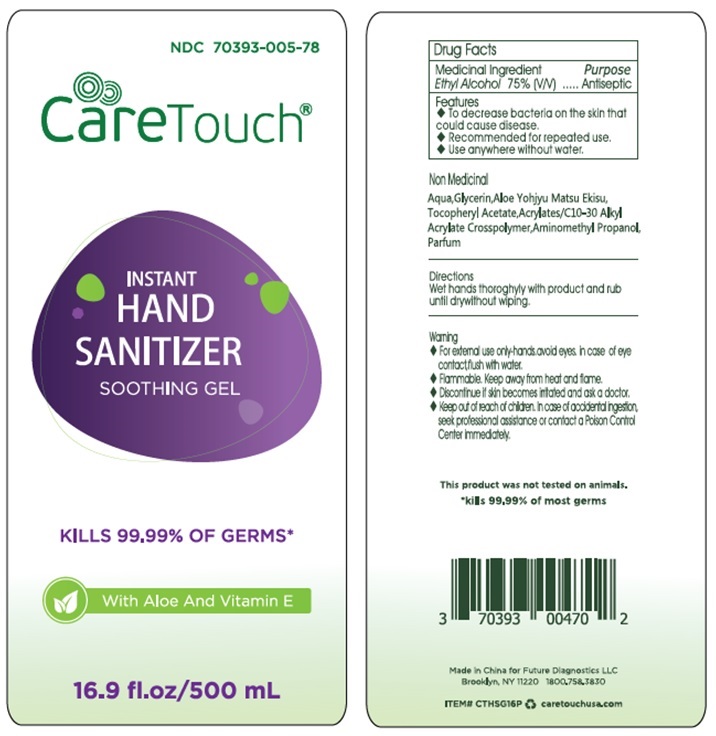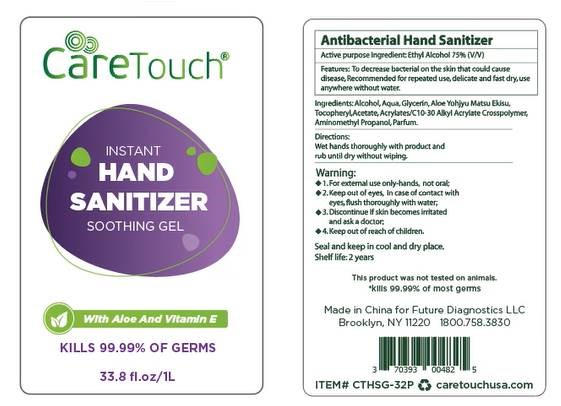 DRUG LABEL: Care Touch INSTANT HAND SANITIZER
NDC: 70393-005 | Form: GEL
Manufacturer: Future Diagnostics Llc
Category: otc | Type: HUMAN OTC DRUG LABEL
Date: 20200729

ACTIVE INGREDIENTS: ALCOHOL 75 mL/100 mL
INACTIVE INGREDIENTS: WATER; GLYCERIN; ALOE VERA LEAF; .ALPHA.-TOCOPHEROL ACETATE; CARBOMER INTERPOLYMER TYPE A (ALLYL SUCROSE CROSSLINKED); AMINOMETHYLPROPANOL

Care Touch INSTANT HAND SANITIZER SOOTHING GEL

Medicinal Ingredient

Ethyl Alcohol 75% (V/V)

Purpose

Antiseptic

Features

- To decrease bacteria on the skin that could cause disease.
- Recommended for repeated use.
- Use anywhere without water.

Warning

- For external use only-hands. avoid eyes. in case of eye contact, flush with water.
- Flammable. Keep away from heat and flame.
- Discontinue if skin becomes irritated and ask a doctor

- Keep out of reach of children. In case of accidental ingestion. seek professional assisstance or control a Poison Control Center immediately.

Directions

Wet hands thoroughly with product and rub until dry without wiping.

Non Medicinal

Aqua, Glycerin, Aloe Yohjyu Matsu Ekisu, Tocopheryl Acetate, Acrylates/C10-30 Alkyl Acrylate Crosspolymer, Aminomethyl Propanol, Parfum

CareTouch®

INSTANT HAND SANITIZER SOOTHING GEL

KILLS 99.99% OF GERMS*

With Aloe And Vitamin E

This product as not tested on animals.

*kills 99.99% of most germs

Made in China for Future Diagnostics LLC

Brooklyn , NY 1120 1800.758.3830

caretouchusa.com